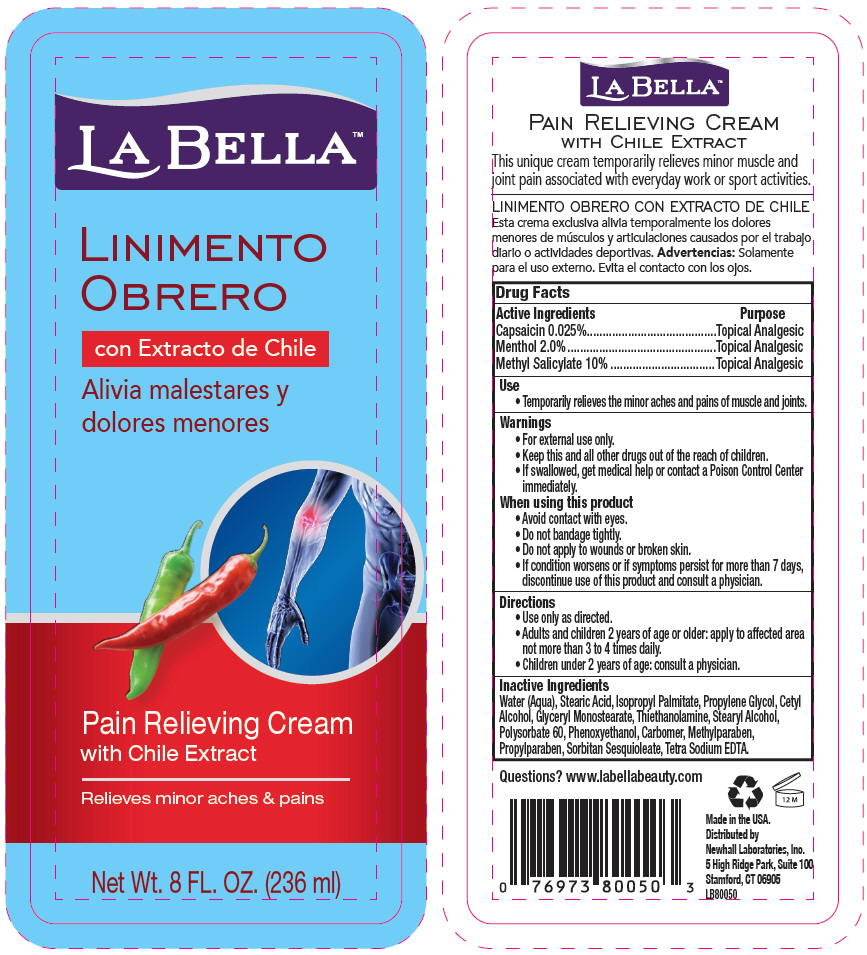 DRUG LABEL: LaBella Linimento Obrero
NDC: 31774-8005 | Form: CREAM
Manufacturer: Golden Sun Inc DBA Newhall Laboratories
Category: otc | Type: HUMAN OTC DRUG LABEL
Date: 20151106

ACTIVE INGREDIENTS: Capsaicin 0.25 mg/1 mL; Menthol, Unspecified Form 20 mg/1 mL; Methyl Salicylate 100 mg/1 mL
INACTIVE INGREDIENTS: Water; Stearic Acid; Isopropyl Palmitate; Propylene Glycol; Cetyl Alcohol; Glyceryl Monostearate; Stearyl Alcohol; Polysorbate 60; Phenoxyethanol; Methylparaben; Propylparaben; Sorbitan Sesquioleate; Edetate Sodium

LaBella™ Linimento Obrero

Drug Facts

ACTIVE INGREDIENT

Active Ingredients | Purpose
Capsaicin 0.025% | Topical Analgesic
Menthol 2.0% | Topical Analgesic
Methyl Salicylate 10% | Topical Analgesic

Use

- Temporarily relieves the minor aches and pains of muscle and joints.

Warnings

KEEP OUT OF REACH OF CHILDREN

- For external use only.
- Keep this and all other drugs out of the reach of children.
- If swallowed, get medical help or contact a Poison Control Center immediately.

When using this product

- Avoid contact with eyes.
- Do not bandage tightly.
- Do not apply to wounds or broken skin.
- If condition worsens or if symptoms persist for more than 7 days, discontinue use of this product and consult a physician.

Directions

- Use only as directed.
- Adults and children 2 years of age or older: apply to affected area not more than 3 to 4 times daily.
- Children under 2 years of age: consult a physician.

Inactive Ingredients

Water (Aqua), Stearic Acid, Isopropyl Palmitate, Propylene Glycol, Cetyl Alcohol, Glyceryl Monostearate, Thiethanolamine, Stearyl Alcohol, Polysorbate 60, Phenoxyethanol, Carbomer, Methylparaben, Propylparaben, Sorbitan Sesquioleate, Tetra Sodium EDTA.

Questions?

www.labellabeauty.com

Distributed by
Newhall Laboratories, Inc.
5 High Ridge Park, Suite 100
Stamford, CT 06905

PRINCIPAL DISPLAY PANEL - 236 ml Bottle Label

LA BELLA™

LINIMENTO
OBRERO

Pain Relieving Cream
with Chile Extract

Relieves minor aches & pains

Net Wt. 8 FL. OZ. (236 ml)